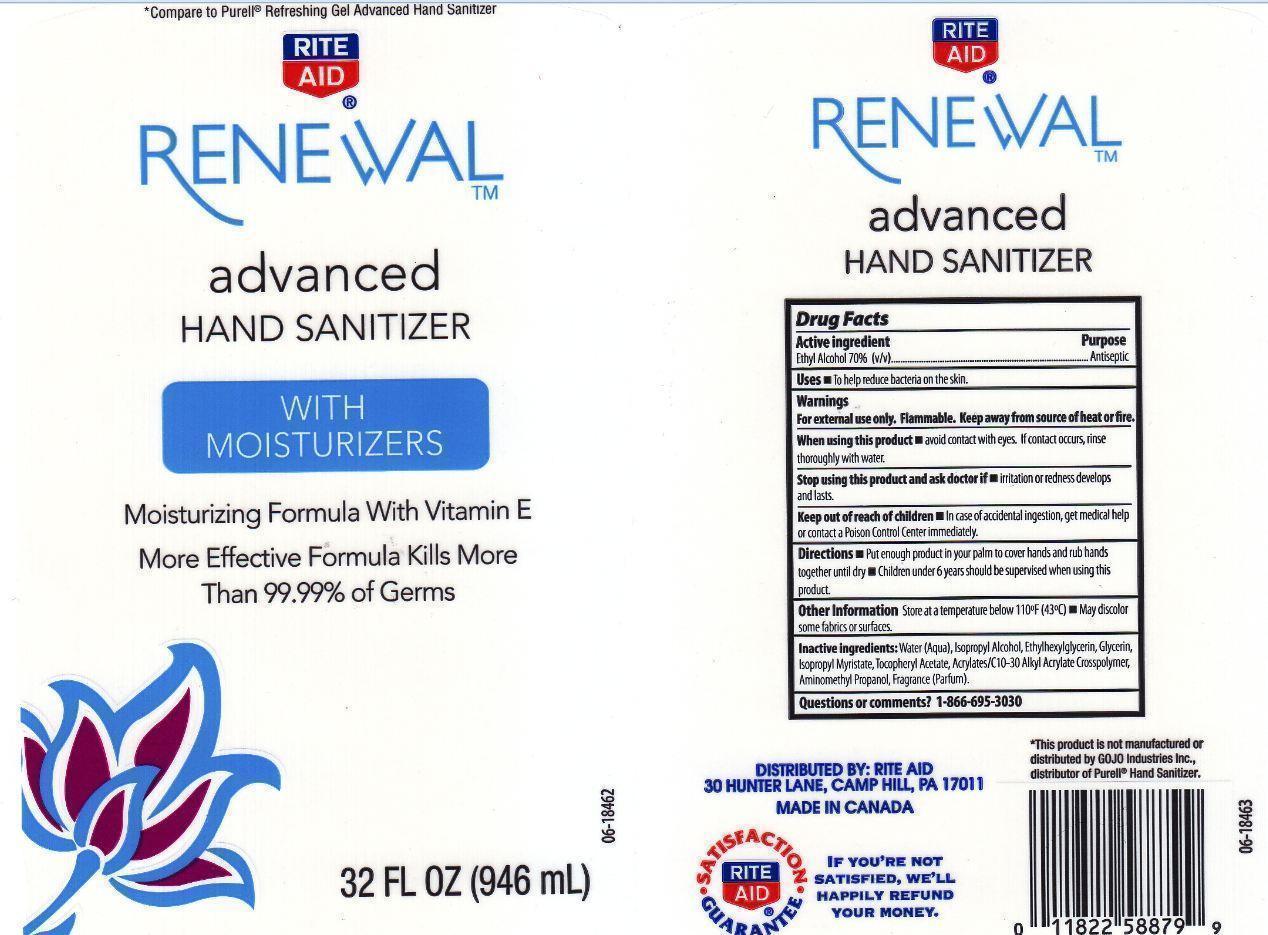 DRUG LABEL: RITE AID RENEWAL
NDC: 11822-4803 | Form: LIQUID
Manufacturer: RITE AID CORPORATION
Category: otc | Type: HUMAN OTC DRUG LABEL
Date: 20130319

ACTIVE INGREDIENTS: ALCOHOL 700 mg/1 mL
INACTIVE INGREDIENTS: WATER; ISOPROPYL ALCOHOL; ETHYLHEXYLGLYCERIN; GLYCERIN; ISOPROPYL MYRISTATE; .ALPHA.-TOCOPHEROL ACETATE; CARBOMER COPOLYMER TYPE A (ALLYL PENTAERYTHRITOL CROSSLINKED); AMINOMETHYLPROPANOL

DRUG FACTS

ACTIVE INGREDIENT

ETHYL ALCOHOL 70% (V/V)

PURPOSE

ANTISEPTIC

USES

TO HELP REDUCE BACTERIA ON THE SKIN.

WARNINGS

FOR EXTERNAL USE ONLY. FLAMABLE. KEEP AWAY FROM SOURCE OF HEAT OR FIRE.

WHEN USING THIS PRODUCT

AVOID CONTACT WITH EYES. IF CONTACT OCCURS, RINSE THOROUGHLY WITH WATER.

STOP USING THIS PRODUCT AND ASK DOCTOR IF

IRRITATION OR REDNESS DEVELOPS AND LASTS.

KEEP OUT OF REACH OF CHILDREN

IN CASE OF ACCIDENTAL INGESTION, GET MEDICAL HELP OR CONTACT A POISON CONTROL CENTER IMMEDIATELY.

DIRECTIONS

PUT ENOUGH PRODUCT IN YOUR PALM TO COVER HANDS AND RUB HANDS TOGETHER UNTIL DRY. CHILDREN UNDER 6 YEARS SHOULD BE SUPERVISED WHEN USING THIS PRODUCT

OTHER INFORMATION

STORE AT A TEMPERATURE BELOW 110F (43C). MAY DISCOLOR SOME FABRICS OR SURFACES.

INACTIVE INGREDIENTS

WATER (AQUA), ISOPROPYL ALCOHOL, ETHYLHEXYLGLYCERIN, GLYCERIN, ISOPROPYL MYRISTATE, TOCOPHERYL ACETATE, ACRYLATES/C10-30 ALKYL ACRYLATE CROSSPOLYMER, AMINOMETHYL PROPANOL, FRAGRANCE (PARFUM).

QUESTIONS OR COMMENTS?

1-866-695-3030